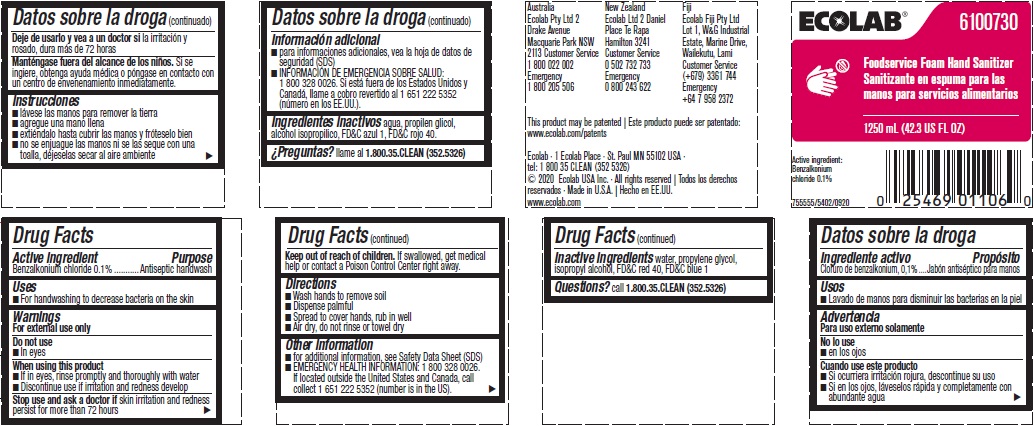 DRUG LABEL: Foodservice Foam Hand Sanitizer
NDC: 47593-470 | Form: SOLUTION
Manufacturer: Ecolab Inc.
Category: otc | Type: HUMAN OTC DRUG LABEL
Date: 20250515

ACTIVE INGREDIENTS: BENZALKONIUM CHLORIDE 0.1 mg/100 mL
INACTIVE INGREDIENTS: WATER; ISOPROPYL ALCOHOL; PROPYLENE GLYCOL; FD&C RED NO. 40; FD&C BLUE NO. 1

Drug Facts

Active ingredient

Benzalkonium chloride 0.1%

Purpose

Antiseptic handwash

INDICATIONS AND USAGE

- for handwashing to decrease bacteria on the skin

Warnings

For external use only

Do not use

- in eyes

When using this product

- if in eyes, rinse promptly and throughly with water
- discontinue use if irritation and redness develop

Stop use and ask doctor if

- skin irritation or redness persists for more than 72 hours

Keep out of reach of children. If swallowed, get medical help or contact a Poison Control Center right away.

Directions

- wash hands to remove soil
- dispense palmful
- spread to cover hands, rub in well
- air dry, do not rinse or towel dry

Other information

- For additional information, see Safety Data Sheet (MSDS)
- EMERGENCY HEALTH INFORMATION: 1 800 328 0026. If located outside the United States and Canada, call collect 1 651 222 5352 (number is in the US).

INACTIVE INGREDIENT

Inactive ingredients water, propylene glycol, isopropyl alcohol, FD&C red 40, FD&C blue1

Questions? call 1-800-35-CLEAN (352-5326)

Principal display panel and representative container

Ecolab

6100730

Foodservice Foam Hand Santiizer

1250 mL (42.3 US FL OZ)

Active ingredient:

Benzalkonium chloride 0.1%

755555/5402/0920

Ecolab - 1 Ecolab Place - St. Paul MN 55102 USA

tel: 1 800 35 CLEAN (352 5326)

(c) 2020 Ecolab USA Inc - All rights reserved

Made in U.S.A.

www.ecolab.com